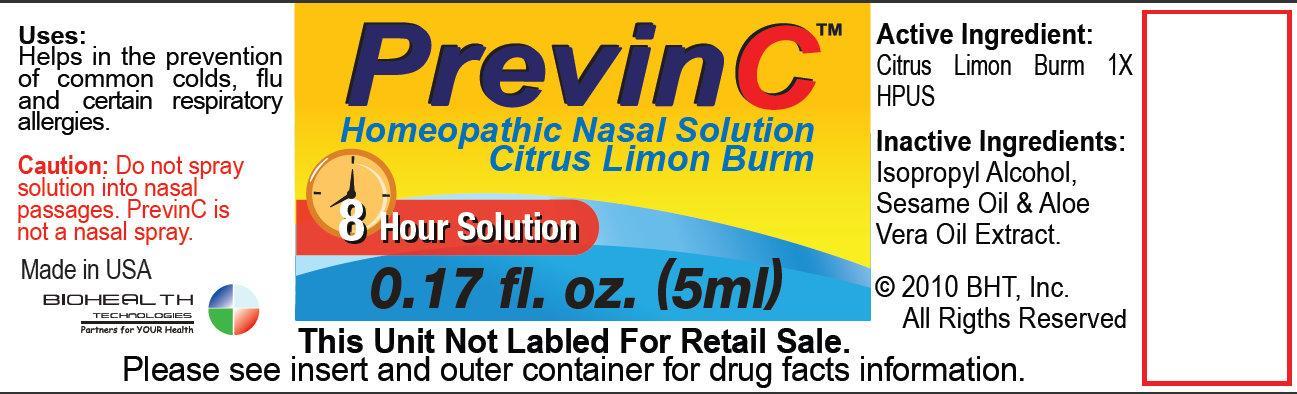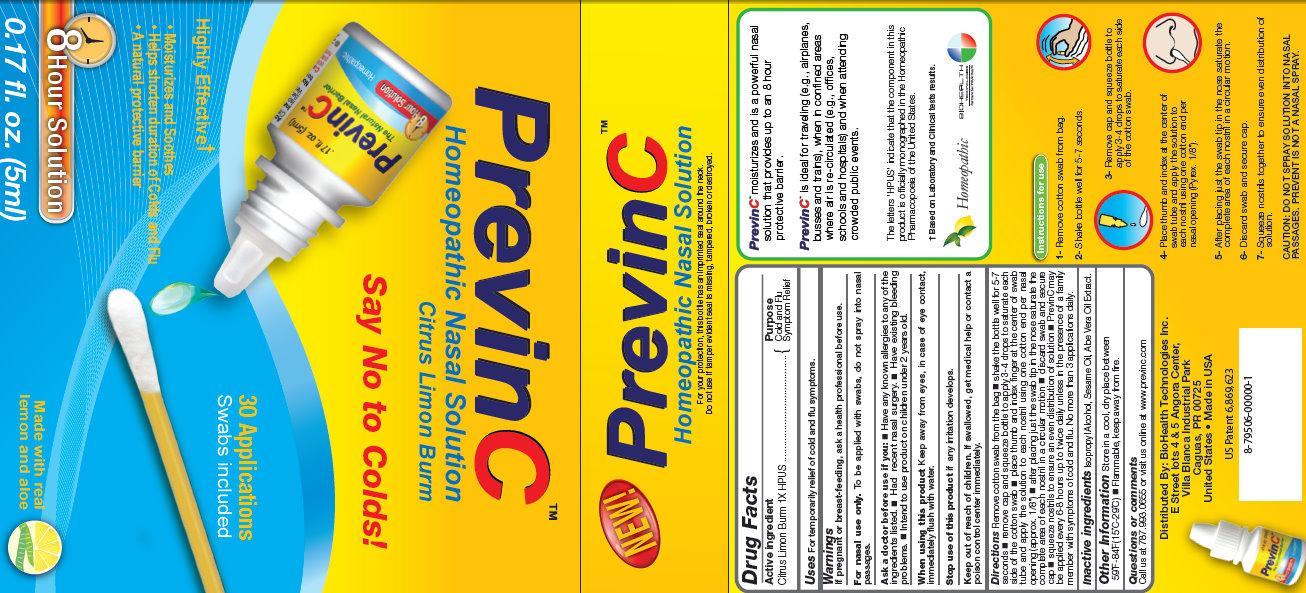 DRUG LABEL: PrevinC
NDC: 28475-810 | Form: SOLUTION
Manufacturer: BioHealth Technologies Inc.
Category: homeopathic | Type: HUMAN OTC DRUG LABEL
Date: 20121116

ACTIVE INGREDIENTS: LEMON 1 [hp_X]/5 mL
INACTIVE INGREDIENTS: ISOPROPYL ALCOHOL; SESAME OIL; ALOE VERA LEAF

PrevinC Homeopathic Nasal Solution

Active Ingredient

Citrus Limon Burm 1X HPUS

Purpose

Cold and Flu Symptom Relief

INDICATIONS AND USAGE

Uses For temporarily relief of cold and flu symptoms

WARNINGS

If pregnant or breast-feeding, ask a health professional before use.

For nasal use only. To be applied with swabs, do not spray into nasal passages.

Ask a doctor before use if you:

- Have any known allergies to any of the ingredients listed.
- Had recent nasal surgery.
- Have existing bleeding problems.
- Intend to use product on children under 2 years old.

When using this product Keep away from eyes, in case of eye contact, immediately flush with water.
Stop use of this product if any irritation develops.

Keep out of reach of children. If swallowed, get medical help or contact a poison control center immediately.

Directions

Remove cotton swab from the bag

- shake the bottle well for 5-7 seconds
- remove cap and squeeze bottle to apply 3-4 drops to saturate each side of the cotton swab
- place thumb and index finger at the center of swab tube and apply solution to each nostril using one cotton end per nasal opening (approx. 1/8")
- after placing just the swab tip in the nose saturate the complete area of each nostril in a circular motion
- discard swab and secure cap
- squeeze nostrils to ensure an even distribution of solution
- PrevinC may be applied every 6-8 hours up to twice daily unless in the presence of a family member with symptoms of cold and flu. No more than 3 applications daily.

Inactive ingredients

Isopropyl Alcohol, Sesame Oil, Aloe Vera Oil Extract

Other Information Store in a cool, dry place between 59 degrees F - 84 degrees F (15 degrees C - 29 degrees C)

- Flammable, keep away from fire

Questions or comments

Call us at 787.993.0655 or visit us online at www.previnc.com

Distributed By: BioHealth Technologies Inc.

E Street lots 4 and 5 Angora Center,

Villa Blanca Industrial Park

Caguas, PR 00725

United States Made in USA

DESCRIPTION

PrevinC moisturizes and is a powerful nasal solution that provides up to an 8 hour protective barrier.

PrevinC is ideal for traveling (e.g., airplanes, busses and trains), when in confined area where air is re-circulated (e.g., offices, schools and hospitals) and when attending crowded public events.

The letters 'HPUS' indicate that the component in this product is officially monographed in the Homeopathic Pharmacopoeia of the United States.

Homeopathic

DESCRIPTION

PrevinC

Homeopathic Nasal Solution

Citrus Limon Burm

Say No to Colds!

Improves your natural protective barriers in the nose!
For the temporary relief of cold and flu symptoms.
Ideal when in:

- Offices
- Schools
- Day Cares
- Hospitals
- Traveling
- Events

Non-Narcotic
PrevinC improves the natural defense function of the nose, which includes filtration and moisture. Should be applied when in contact with someone with a cold, flu, or when air is recirculated.
8 Hour Solution
PrevinC moisturizes and is a powerful nasal solution that provides up to an 8 hour protective barrier.
PrevinC is designed for Topical USE ONLY, no warranty, either expressed or inferred is given for usage contrary to the instructions.
PrevinC may be applied every 6-8 hours up to twice daily unless in the presence of a family member with symptoms of cold and flu. No more than 3 applications daily.
It is preferred that you blow your nose prior to application if it is stuffy.If you need blow your nose after PrevinC has been applied, then re-apply the solution. Do not exceed 3 applications daily.
Made with real lemon and aloe
Homeopathic
For your protection, this bottle has an imprinted seal around the neck.
Do not use if tamper evident seal is missing, tampered, broken or destroyed.

PACKAGE LABEL

PrevinC

Homeopathic Nasal Solution

Citrus Limon Burm

Say No to Colds!

8 Hour Solution

0.17 fl. oz (5ml)